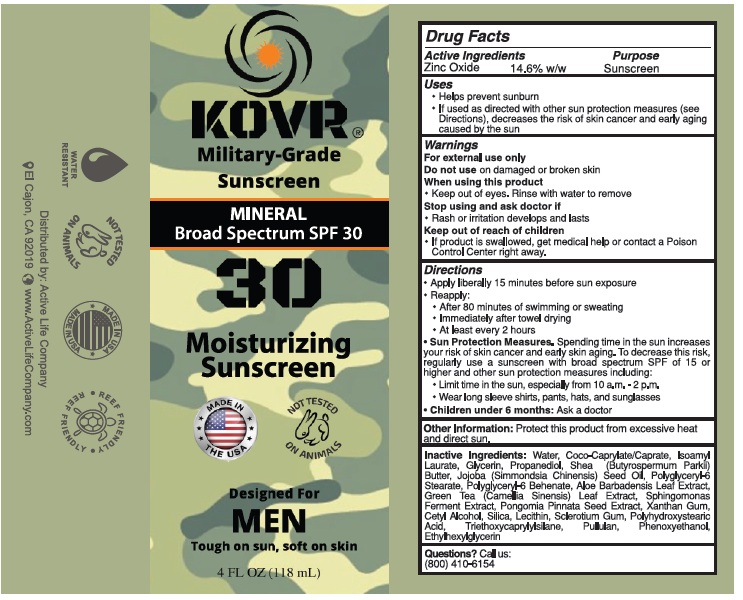 DRUG LABEL: KOVR Military grade sunscreen for Men
NDC: 83531-502 | Form: LOTION
Manufacturer: ACTIVE LIFE INC
Category: otc | Type: HUMAN OTC DRUG LABEL
Date: 20251126

ACTIVE INGREDIENTS: ZINC OXIDE 14.6 g/100 g
INACTIVE INGREDIENTS: WATER; COCOYL CAPRYLOCAPRATE; ISOAMYL LAURATE; GLYCERIN; PROPANEDIOL; SHEA BUTTER; JOJOBA OIL; POLYGLYCERYL-6 STEARATE; ALOE VERA LEAF JUICE; GREEN TEA LEAF; PONGAMIA PINNATA SEED; XANTHAN GUM; CETYL ALCOHOL; SILICON DIOXIDE; SOYBEAN LECITHIN; BETASIZOFIRAN; POLYHYDROXYSTEARIC ACID (2300 MW); TRIETHOXYCAPRYLYLSILANE; PULLULAN; ETHYLHEXYLGLYCERIN; PHENOXYETHANOL; FERMENT COMPLEX 6/PF; POLYGLYCERYL-6 BEHENATE

Active Ingredients

Zinc Oxide 14.6% w/w

Purpose

Sunscreen

Uses:

- Helps prevent sunburn
- If used as directed with other sun protection measures (see Directions), decreases the risk of skin cancer and early aging caused by the sun

Warnings

For external use only.

Do not use on damaged or broken skin

When using this product
• Keep out of eyes. Rinse with water to remove

Stop use and ask doctor if
• Rash or irritation develops and lasts

Keep out of reach of children
• If the product is swallowed, get medical help or contact a Poison Control Center right away.

Directions:

Apply liberally 15 minutes before sun exposure Reapply:
• After 80 minutes of swimming or sweating
• Immediately after towel drying
• At least every 2 hours
Sun Protection Measures. Spending time in the sun increases your risk of skin cancer and early skin aging. To decrease this risk, regularly use a sunscreen with a broad spectrum SPF of 15 or higher and other sun protection measures, including:
• Limit time in the sun, especially from 10 a.m. – 2 p.m.
• Wear long sleeve shirts, pants, hats, and sunglasses
• Children under 6 months: Ask a doctor

Other Information:

Protect this product from excessive heat and direct sun

Inactive Ingredients:

Water, Coco-Caprylate/Caprate, Isoamyl Laurate, Glycerin, Propanediol, Shea Butter, Jojoba Seed Oil, Polyglyceryl-6 Stearate, Aloe Barbadensis Leaf Extract, Green Tea Leaf Extract, Sphingomonas Ferment Extract, Pongomia Pinnata Seed Extract, Xanthan Gum, Cetyl Alcohol, Silica, Lecithin, Sclerotium Gum, Polyhydroxystearic Acid, Triethoxycaprylylsilane, Pullulan, Phenoxyethanol, Ethylhexylglycerin

Questions?

Call us : (800) 410-6154